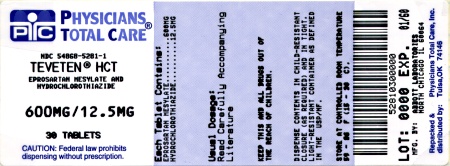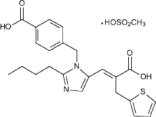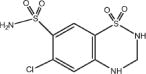 DRUG LABEL: Teveten HCT
NDC: 54868-5281 | Form: TABLET
Manufacturer: Physicians Total Care, Inc.
Category: prescription | Type: HUMAN PRESCRIPTION DRUG LABEL
Date: 20120103

ACTIVE INGREDIENTS: EPROSARTAN MESYLATE 600 mg/1 1; HYDROCHLOROTHIAZIDE 12.5 mg/1 1
INACTIVE INGREDIENTS: CELLULOSE, MICROCRYSTALLINE; LACTOSE MONOHYDRATE; STARCH, CORN; CROSPOVIDONE; MAGNESIUM STEARATE; WATER; POLYETHYLENE GLYCOL 3350; TALC; POLYVINYL ALCOHOL; TITANIUM DIOXIDE; FERRIC OXIDE YELLOW; FERROSOFERRIC OXIDE

TEVETEN® HCT
(eprosartan mesylate/hydrochlorothiazide)600/12.5mg 600/25mg

Rx Only

USE IN PREGNANCY

When used in pregnancy during the second and third trimesters, drugs that act directly on the renin-angiotensin system can cause injury and even death to the developing fetus. When pregnancy is detected, TEVETEN® HCT Tablets should be discontinued as soon as possible. See WARNINGS: Fetal/Neonatal Morbidity and Mortality.

DESCRIPTION

TEVETEN® HCT 600/12.5 mg and TEVETEN® HCT 600/25 mg (eprosartan mesylate-hydrochlorothiazide) combine an angiotensin II receptor (AT1 subtype) antagonist and a diuretic, hydrochlorothiazide. TEVETEN® (eprosartan mesylate) is a non-biphenyl non-tetrazole angiotensin II receptor (AT1) antagonist. A selective non-peptide molecule, TEVETEN® is chemically described as the monomethanesulfonate of (E)-2-butyl-1-(p-carboxybenzyl)-α-2-thienylmethylimidazole-5-acrylic acid. Its empirical formula is C23H24N2O4S•CH4O3S and molecular weight is 520.625. Its structural formula is:

Eprosartan mesylate is a white to off-white free-flowing crystalline powder that is insoluble in water, freely soluble in ethanol, and melts between 248°C and 250°C. Hydrochlorothiazide is 6-chloro-3,4-dihydro-2 H 1,2,4-benzothiadiazine-7-sulfonamide 1,1-dioxide. Its empirical formula is C7H8ClN3O4S2 and its structural formula is:

Hydrochlorothiazide is a white, or practically white, crystalline powder with a molecular weight of 297.74, which is slightly soluble in water, but freely soluble in sodium hydroxide solution. TEVETEN® HCT is available for oral administration in film-coated, non-scored, capsule-shaped tablet combinations of eprosartan mesylate and hydrochlorothiazide. TEVETEN® HCT 600/12.5 mg contains 735.8 mg of eprosartan mesylate (equivalent to 600 mg eprosartan) and 12.5 mg hydrochlorothiazide in a butterscotch-colored tablet. TEVETEN® HCT 600/25 mg contains 735.8 mg of eprosartan mesylate (equivalent to 600 mg eprosartan) and 25 mg hydrochlorothiazide in a brick-red tablet. Inactive ingredients of both tablets: microcrystalline cellulose, lactose monohydrate, pregelatinized starch, crospovidone, magnesium stearate, and purified water. Ingredients of the OPADRY® 85F27320 butterscotch film coating: polyethylene glycol 3350, talc, polyvinyl alcohol, titanium dioxide, iron oxide black, and iron oxide yellow. Ingredients of the OPADRY® II 85F24297 pink film coating: polyethylene glycol 3350, titanium dioxide, talc, polyvinyl alcohol, iron oxide red, and iron oxide yellow.

CLINICAL PHARMACOLOGY

Mechanism of Action

Eprosartan: Angiotensin II (formed from angiotensin I in a reaction catalyzed by angiotensin-converting enzyme [kininase II]), a potent vasoconstrictor, is the principal pressor agent of the renin-angiotensin system. Angiotensin II also stimulates aldosterone synthesis and secretion by the adrenal cortex, cardiac contraction, renal resorption of sodium, activity of the sympathetic nervous system, and smooth muscle cell growth. Eprosartan blocks the vasoconstrictor and aldosterone-secreting effects of angiotensin II by selectively blocking the binding of angiotensin II to the AT1 receptor found in many tissues (e.g., vascular smooth muscle, adrenal gland). There is also an AT2 receptor found in many tissues but it is not known to be associated with cardiovascular homeostasis. Eprosartan does not exhibit any partial agonist activity at the AT1 receptor. Its affinity for the AT1 receptor is 1,000 times greater than for the AT2 receptor. In vitro binding studies indicate that eprosartan is a reversible, competitive inhibitor of the AT1 receptor. Blockade of the AT1 receptor removes the negative feedback of angiotensin II on renin secretion, but the resulting increased plasma renin activity and circulating angiotensin II do not overcome the effect of eprosartan on blood pressure. TEVETEN® HCT does not inhibit kininase II, the enzyme that converts angiotensin I to angiotensin II and degrades bradykinin; whether this has clinical relevance is not known. It does not bind to or block other hormone receptors or ion channels known to be important in cardiovascular regulation.

Hydrochlorothiazide: Hydrochlorothiazide is a thiazide diuretic. Thiazides affect the renal tubular mechanisms of electrolyte reabsorption, directly increasing excretion of sodium and chloride in approximately equivalent amounts. Indirectly, the diuretic action of hydrochlorothiazide reduces plasma volume, with consequent increases in plasma renin activity, increases in aldosterone secretion, increases in urinary potassium loss, and decreases in serum potassium. The renin-aldosterone link is mediated by angiotensin II, so coadministration of an angiotensin II receptor antagonist tends to reverse the potassium loss associated with these diuretics. The mechanism of the antihypertensive effect of thiazides is unknown.

Pharmacokinetics

General

Eprosartan: Absolute bioavailability following a single 300-mg oral dose of eprosartan is approximately 13%. Eprosartan plasma concentrations peak at 1 to 2 hours after an oral dose in the fasted state. Administering eprosartan with food delays absorption, and causes variable changes (<25%) in Cmax and AUC values which do not appear clinically important. Plasma concentrations of eprosartan increase in a slightly less than dose-proportional manner over the 100 mg to 800 mg dose range. The mean terminal elimination half-life of eprosartan following multiple oral doses of 600 mg was approximately 20 hours. Eprosartan does not significantly accumulate with chronic use.

Hydrochlorothiazide: When hydrochlorothiazide plasma levels have been followed for at least 24 hours, the plasma half-life has been observed to vary between 5.6 and 14.8 hours.

Metabolism and Excretion:

Eprosartan: Eprosartan is eliminated by biliary and renal excretion, primarily as unchanged compound. Less than 2% of an oral dose is excreted in the urine as a glucuronide. There are no active metabolites following oral and intravenous dosing with [^14C] eprosartan in human subjects. Eprosartan was the only drug-related compound found in the plasma and feces. Following intravenous [^14C] eprosartan, about 61% of the material is recovered in the feces and about 37% in the urine. Following an oral dose of [^14C] eprosartan, about 90% is recovered in the feces and about 7% in the urine. Approximately 20% of the radioactivity excreted in the urine was an acyl glucuronide of eprosartan with the remaining 80% being unchanged eprosartan. Eprosartan is not metabolized by cytochrome P450 enzymes.

Hydrochlorothiazide: Hydrochlorothiazide is not metabolized but is eliminated rapidly by the kidney. At least 61% of the oral dose is eliminated unchanged within 24 hours.

Distribution

Eprosartan: Plasma protein binding of eprosartan is high (approximately 98%) and constant over the concentration range achieved with therapeutic doses. The pooled population pharmacokinetic analysis from two Phase 3 trials of 299 men and 172 women with mild to moderate hypertension (aged 20 to 93 years) showed that eprosartan exhibited a population mean oral clearance (CL/F) for an average 60-year-old patient of 48.5 L/hr. The population mean steady-state volume of distribution (Vss/F) was 308 L. Eprosartan pharmacokinetics were not influenced by weight, race, gender or severity of hypertension at baseline. Oral clearance was shown to be a linear function of age with CL/F decreasing 0.62 L/hr for every year increase.

Hydrochlorothiazide: Hydrochlorothiazide crosses the placental but not the blood-brain barrier and it is excreted in breast milk.

Special Populations

Pediatric: Eprosartan pharmacokinetics have not been investigated in patients younger than 18 years of age.

Geriatric: Following single oral dose administration of eprosartan to healthy elderly men, (aged 68 to 78 years), AUC, Cmax, and Tmax eprosartan values increased, on average, by approximately twofold, compared to healthy young men (aged 20 to 38 years) who received the same dose. The extent of plasma protein binding is not influenced by age.

Gender: There was no difference in the pharmacokinetics and plasma protein binding between men and women following single oral dose administration of eprosartan.

Race: A pooled population pharmacokinetic analysis of 442 Caucasian and 29 non-Caucasian hypertensive patients showed that oral clearance and steady-state volume of distribution were not influenced by race.

Renal Insufficiency: Following administration of 600 mg once daily, there was a 70-90% increase in AUC, and a 30-50% increase in Cmax in moderate or severe renal impairment. The unbound eprosartan fractions increased by 35% and 59% in patients with moderate and severe renal impairment, respectively. No initial dosing adjustment is generally necessary in patients with moderate or severe renal impairment, with maximum dose not exceeding 600 mg daily. Eprosartan was poorly removed by hemodialysis (CLHD<1L/hr) (see DOSAGE AND ADMINISTRATION).

Hepatic Insufficiency: Eprosartan AUC (but not Cmax) values increased, on average, by approximately 40% in men with decreased hepatic function compared to healthy men after a single 100 mg oral dose of eprosartan. The extent of eprosartan plasma protein binding was not influenced by hepatic dysfunction. No dosage adjustment is necessary for patients with hepatic impairment.

Drug Interactions

Eprosartan: Concomitant administration of eprosartan with digoxin had no effect on a single oral-dose digoxin pharmacokinetics. Concomitant administration of eprosartan and warfarin had no effect on steady-state prothrombin time ratios (INR) in healthy volunteers. Concomitant administration of eprosartan and glyburide in diabetic patients did not affect 24-hour plasma glucose profiles. Eprosartan pharmacokinetics were not affected by concomitant administration of ranitidine. Eprosartan did not inhibit human cytochrome P450 enzymes CYP1A, 2A6, 2C9/8, 2C19, 2D6, 2E, and 3A in vitro. Eprosartan steady-state plasma concentrations were not affected by concomitant administration of ketoconazole or fluconazole, potent inhibitors of CYP3A and 2C9, respectively.

Eprosartan-Hydrochlorothiazide: There is no pharmacokinetic interaction between 600 mg eprosartan and 12.5 mg hydrochlorothiazide.

Pharmacodynamics and Clinical Effects

Eprosartan: Eprosartan inhibits the pharmacologic effects of angiotensin II infusions in healthy adult men. Single oral doses of eprosartan from 10 mg to 400 mg have been shown to inhibit the vasopressor, renal vasoconstrictive and aldosterone secretory effects of infused angiotensin II with complete inhibition evident at doses of 350 mg and above. Eprosartan inhibits the pressor effects of angiotensin II infusions. A single oral dose of 350 mg of eprosartan inhibits pressor effects by approximately 100% at peak, with approximately 30% inhibition persisting for 24 hours. The absence of angiotensin II AT1 agonist activity has been demonstrated in healthy adult men. In hypertensive patients treated chronically with eprosartan, there was a twofold rise in angiotensin II plasma concentration and a twofold rise in plasma renin activity, while plasma aldosterone levels remained unchanged. Serum potassium levels also remained unchanged in these patients. Achievement of maximal blood pressure response to a given dose in most patients may take 2 to 3 weeks of treatment. Onset of blood pressure reduction is seen within 1 to 2 hours of dosing with few instances of orthostatic hypotension. Blood pressure control is maintained with once- or twice-daily dosing over a 24-hour period. Discontinuing treatment with eprosartan does not lead to a rapid rebound increase in blood pressure. There was no change in mean heart rate in patients treated with eprosartan in controlled clinical trials. Eprosartan increases mean effective renal plasma flow (ERPF) in salt-replete and salt-restricted normal subjects. A dose-related increase in ERPF of 25% to 30% occurred in salt-restricted normal subjects, with the effect plateauing between 200 mg and 400 mg doses. There was no change in ERPF in hypertensive patients and patients with renal insufficiency on normal salt diets. Eprosartan did not reduce glomerular filtration rate in patients with renal insufficiency or in patients with hypertension, after 7 days and 28 days of dosing, respectively. In hypertensive patients and patients with chronic renal insufficiency, eprosartan did not change fractional excretion of sodium and potassium. Eprosartan (1200 mg once daily for 7 days or 300 mg twice daily for 28 days) had no effect on the excretion of uric acid in healthy men, patients with essential hypertension or those with varying degrees of renal insufficiency. There were no effects on mean levels of fasting triglycerides, total cholesterol, HDL cholesterol, LDL cholesterol or fasting glucose.

Clinical Trials

Eprosartan Mesylate: The safety and efficacy of TEVETEN® has been evaluated in controlled clinical trials worldwide that enrolled predominantly hypertensive patients with sitting DBP ranging from 95 mmHg to ≤115 mmHg. There is also some experience with use of eprosartan together with other antihypertensive drugs in more severe hypertension. The antihypertensive effects of TEVETEN® were demonstrated principally in five placebo-controlled trials (4 to 13 weeks' duration) including dosages of 400 mg to 1200 mg given once daily (two studies), 25 mg to 400 mg twice daily (two studies), and one study comparing total daily doses of 400 mg to 800 mg given once daily or twice daily. The five studies included 1,111 patients randomized to eprosartan and 395 patients randomized to placebo. The studies showed dose-related antihypertensive responses. At study endpoint, patients treated with TEVETEN® at doses of 600 mg to 1200 mg given once daily experienced significant decreases in sitting systolic and diastolic blood pressure at trough, with differences from placebo of approximately 5-10/3-6 mmHg. Limited experience is available with the dose of 1200 mg administered once daily. In a direct comparison of 200 mg to 400 mg b.i.d. with 400 mg to 800 mg q.d. of TEVETEN®, effects at trough were similar. Patients treated with TEVETEN® at doses of 200 mg to 400 mg given twice daily experienced significant decreases in sitting systolic and diastolic blood pressure at trough, with differences from placebo of approximately 7-10/4-6 mmHg. Peak (1 to 3 hours) effects were uniformly, but moderately, larger than trough effects with b.i.d. dosing, with the trough-to-peak ratio for diastolic blood pressure 65% to 80%. In the once-daily dose-response study, trough-to-peak responses of ≤50% were observed at some doses (including 1200 mg), suggesting attenuation of effect at the end of the dosing interval. The antihypertensive effect of TEVETEN® was similar in men and women, but was somewhat smaller in patients over 65. There were too few black subjects to determine whether their response was similar to Caucasians. In general, blacks (usually a low renin population) have had smaller responses to ACE inhibitors and angiotensin II inhibitors than Caucasian populations. Angiotensin-converting enzyme (ACE) inhibitor-induced cough (a dry, persistent cough) can lead to discontinuation of ACE inhibitor therapy. In one study, patients who had previously coughed while taking an ACE inhibitor were treated with eprosartan, an ACE inhibitor (enalapril) or placebo for six weeks. The incidence of dry, persistent cough was 2.2% on eprosartan, 4.4% on placebo, and 20.5% on the ACE inhibitor; p=0.008 for the comparison of eprosartan with enalapril. In a second study comparing the incidence of cough in 259 patients treated with eprosartan to 261 patients treated with the ACE inhibitor enalapril, the incidence of dry, persistent cough in eprosartan-treated patients (1.5%) was significantly lower (p=0.018) than that observed in patients treated with the ACE inhibitor (5.4%). In addition, analysis of overall data from six double-blind clinical trials involving 1,554 patients showed an incidence of spontaneously reported cough in patients treated with eprosartan of 3.5%, similar to placebo (2.6%).

Hydrochlorothiazide: After oral administration of hydrochlorothiazide, diuresis begins within 2 hours, peaks in about 4 hours, and lasts about 6 to 12 hours.

Eprosartan Mesylate – Hydrochlorothiazide: Four adequate and well-controlled studies were conducted to assess the antihypertensive effectiveness of TEVETEN HCT®/(Eprosartan Mesylate/ hydrochlorothiazide) in 1457 patients with mild-to-moderate essential hypertension. In a 2x2 factorial study with 112-119 hypertensive patients per arm, the mean baseline- and placebo-subtracted reductions in blood pressure at 8 weeks were 3.6/2.1 mmHg on eprosartan 600 mg, 5.6/1.9 mmHg on hydrochlorothiazide 12.5 mg, and 10.0/5.0 mmHg on the combination.

INDICATIONS AND USAGE

TEVETEN® HCT is indicated for the treatment of hypertension. It may be used alone or in combination with other antihypertensives such as calcium channel blockers. This fixed dose combination is not indicated for initial therapy (see DOSAGE AND ADMINISTRATION).

CONTRAINDICATIONS

TEVETEN® HCT is contraindicated in patients who are hypersensitive to this product or any of its components. Because of the hydrochlorothiazide component, this product is contraindicated in patients with anuria or hypersensitivity to other sulfonamide-derived drugs.

WARNINGS

Fetal/Neonatal Morbidity and Mortality

Drugs that act directly on the renin-angiotensin system can cause fetal and neonatal morbidity and death when administered to pregnant women. Several dozen cases have been reported in the world literature in patients who were taking angiotensin-converting enzyme inhibitors. When pregnancy is detected, TEVETEN® HCT should be discontinued as soon as possible. The use of drugs that act directly on the renin-angiotensin system during the second and third trimesters of pregnancy has been associated with fetal and neonatal injury, including hypotension, neonatal skull hypoplasia, anuria, reversible or irreversible renal failure, and death. Oligohydramnios has also been reported, presumably resulting from decreased fetal renal function; oligohydramnios in this setting has been associated with fetal limb contractures, craniofacial deformation, and hypoplastic lung development. Prematurity, intrauterine growth retardation, and patent ductus arteriosus have also been reported, although it is not clear whether these occurrences were due to exposure to the drug. These adverse effects do not appear to have resulted from intrauterine drug exposure that has been limited to the first trimester. Mothers whose embryos and fetuses are exposed to an angiotensin II receptor antagonist only during the first trimester should be so informed. Nonetheless, when patients become pregnant, physicians should advise the patient to discontinue the use of eprosartan as soon as possible. Rarely (probably less often than once in every thousand pregnancies), no alternative to a drug acting on the renin-angiotensin system will be found. In these rare cases, the mothers should be apprised of the potential hazards to their fetuses, and serial ultrasound examinations should be performed to assess the intra-amniotic environment. If oligohydramnios is observed, TEVETEN® HCT should be discontinued unless it is considered life-saving for the mother. Contraction stress testing (CST), a nonstress test (NST) or biophysical profiling (BPP) may be appropriate, depending upon the week of pregnancy. Patients and physicians should be aware, however, that oligohydramnios may not appear until after the fetus has sustained irreversible injury. Infants with histories of in utero exposure to an angiotensin II receptor antagonist should be closely observed for hypotension, oliguria, and hyperkalemia. If oliguria occurs, attention should be directed toward support of blood pressure and renal perfusion. Exchange transfusion or dialysis may be required as means of reversing hypotension and/or substituting for disordered renal function. Eprosartan mesylate, alone or in combination with hydrochlorothiazide, has been shown to produce maternal and fetal toxicities (maternal and fetal mortality, low maternal body weight and food consumption, resorptions, abortions and litter loss) in pregnant rabbits given oral doses as low as 10 mg eprosartan/kg/day and 3 mg hydrochlorothiazide/kg/day. No maternal or fetal adverse effects were observed in rabbits at 3 mg eprosartan/kg/day alone or in combination with 1 mg/kg/day of hydrochlorothiazide; this oral dose yielded a systemic exposure (AUC) to unbound eprosartan approximately equal to the human systemic exposure achieved with the dose of eprosartan mesylate contained in the maximum recommended human dose of TEVETEN® HCT (600 mg eprosartan/day). No adverse effects on in utero or postnatal development and maturation of offspring were observed when eprosartan mesylate was administered to pregnant rats at oral doses up to 1000 mg eprosartan/kg/day (the 1000 mg eprosartan/kg/day dose in non-pregnant rats yielded systemic exposure to unbound eprosartan approximately 0.8 times the exposure achieved in humans given 600 mg/day). Thiazides cross the placental barrier and appear in cord blood. There is a risk of fetal or neonatal jaundice, thrombocytopenia, and possibly other adverse reactions that have occurred in adults.

Hypotension in Volume- and/or Salt-Depleted Patients

In patients with an activated renin-angiotensin system, such as volume- and/or salt-depleted patients (e.g., those being treated with diuretics), symptomatic hypotension may occur. These conditions should be corrected prior to administration of TEVETEN® HCT, or the treatment should start under close medical supervision. If hypotension occurs, the patient should be placed in the supine position and, if necessary, given an intravenous infusion of normal saline. A transient hypotensive response is not a contraindication to further treatment, which usually can be continued without difficulty once the blood pressure has stabilized.

Hydrochlorothiazide

Impaired Hepatic Function: Thiazides should be used with caution in patients with impaired hepatic function or progressive liver disease, since minor alterations of fluid and electrolyte balance may precipitate hepatic coma.

Hypersensitivity Reactions: Hypersensitivity reactions to hydrochlorothiazide may occur in patients with or without a history of allergy or bronchial asthma, but are more likely in patients with such a history.

Acute Myopia and Secondary Angle-Closure Glaucoma

Hydrochlorothiazide, a sulfonamide, can cause an idiosyncratic reaction, resulting in acute transient myopia and acute angle-closure glaucoma. Symptoms include acute onset of decreased visual acuity or ocular pain and typically occur within hours to weeks of drug initiation. Untreated acute angle-closure glaucoma can lead to permanent vision loss. The primary treatment is to discontinue hydrochlorothiazide as rapidly as possible. Prompt medical or surgical treatments may need to be considered if the intraocular pressure remains uncontrolled. Risk factors for developing acute angle-closure glaucoma may include a history of sulfonamide or penicillin allergy.

Systemic Lupus Erythematosus: Thiazide diuretics have been reported to cause exacerbation or activation of systemic lupus erythematosus. Lithium Interaction: Lithium generally should not be given with thiazides (see PRECAUTIONS, Drug Interactions, Hydrochlorothiazide, Lithium).

PRECAUTIONS

General

Hyperuricemia may occur or frank gout may be precipitated in certain patients receiving thiazide therapy. Thiazides have been shown to increase the urinary excretion of magnesium; this may result in hypomagnesemia. Thiazides may decrease urinary calcium excretion. Thiazides may cause intermittent and slight elevation of serum calcium in the absence of known disorders of calcium metabolism. Marked hypercalcemia may be evidence of hidden hyperparathyroidism. Thiazides should be discontinued before carrying out tests for parathyroid function. In diabetic patients, dosage adjustment of insulin or oral hypoglycemic agents may be required. Hyperglycemia may occur with thiazide diuretics. Thus, latent diabetes mellitus may become manifest during thiazide therapy. The antihypertensive effects of hydrochlorothiazide may be enhanced in postsympathectomy patients.

Electrolyte Imbalance

Periodic determination of serum electrolytes to detect possible electrolyte imbalance should be performed at appropriate intervals. All patients receiving thiazide therapy should be observed for clinical signs of fluid or electrolyte imbalance: hyponatremia, hypochloremic alkalosis, and hypokalemia. Serum and urine electrolyte determinations are particularly important when the patient is vomiting excessively or receiving parenteral fluids. Warning signs or symptoms of fluid and electrolyte imbalance, irrespective of cause, include: dryness of mouth, thirst, weakness, lethargy, drowsiness, restlessness, confusion, seizures, muscle pains or cramps, muscular fatigue, hypotension, oliguria, tachycardia, and gastrointestinal disturbances such as nausea and vomiting. Hypokalemia may develop, especially with brisk diuresis, when severe cirrhosis is present, or after prolonged therapy. Interference with adequate oral electrolyte intake will also contribute to hypokalemia. Hypokalemia may cause cardiac arrhythmia and may also sensitize or exaggerate the response of the heart to the toxic effects of digitalis (e.g., increased ventricular irritability). Although any chloride deficit is generally mild and usually does not require specific treatment except under extraordinary circumstances (as in liver disease or renal disease), chloride replacement may be required in the treatment of metabolic alkalosis. Dilutional hyponatremia may occur in edematous patients in hot weather; appropriate therapy is water restriction, rather than administration of salt except in rare instances when the hyponatremia is life-threatening. In actual salt depletion, appropriate replacement is the therapy of choice.

Risk of Renal Impairment

As a consequence of inhibiting the renin-angiotensin-aldosterone system, changes in renal function have been reported in susceptible individuals treated with angiotensin II antagonists; in some patients, these changes in renal function were reversible upon discontinuation of therapy. In patients whose renal function may depend on the activity of the renin-angiotensin-aldosterone system (e.g., patients with severe congestive heart failure), treatment with angiotensin-converting enzyme inhibitors and angiotensin II receptor antagonists has been associated with oliguria and/or progressive azotemia and (rarely) with acute renal failure and/or death. TEVETEN® HCT would be expected to behave similarly. In studies of ACE inhibitors in patients with unilateral or bilateral renal artery stenosis, increases in serum creatinine or BUN have been reported. Similar effects have been reported with angiotensin II antagonists; in some patients, these effects were reversible upon discontinuation of therapy. Thiazides should be used with caution in severe renal disease. In patients with renal disease, thiazides may precipitate azotemia. Cumulative effects of the drug may develop in patients with impaired renal function. If progressive renal impairment becomes evident, consider withholding or discontinuing diuretic therapy.

Information for Patients

Pregnancy: Female patients of childbearing age should be told about the consequences of second- and third-trimester exposure to drugs that act on the renin-angiotensin system, and they should also be told that these consequences do not appear to have resulted from intrauterine drug exposure that has been limited to the first trimester. These patients should be asked to report pregnancies to their physicians as soon as possible so that treatment may be discontinued under medical supervision.

Symptomatic Hypotension: A patient receiving TEVETEN® HCT should be cautioned that lightheadedness can occur, especially during the first days of therapy, and that it should be reported to the prescribing physician. The patient should be told that if syncope occurs, TEVETEN® HCT should be discontinued until the physician has been consulted. All patients should be cautioned that inadequate fluid intake, excessive perspiration, diarrhea, or vomiting can lead to an excessive fall in blood pressure, with the same consequences of lightheadedness and possible syncope.

Potassium Supplements: A patient receiving TEVETEN® HCT should be told not to use potassium supplements or salt substitutes containing potassium without consulting the prescribing physician (see PRECAUTIONS, Drug Interactions, Eprosartan Mesylate).

Drug Interactions

Eprosartan Mesylate: Eprosartan has been shown to have no effect on the pharmacokinetics of digoxin and the pharmacodynamics of warfarin and glyburide. Thus, no dosing adjustments are necessary during concomitant use with these agents. Because eprosartan is not metabolized by the cytochrome P450 system, inhibitors of CYP450 enzyme would not be expected to affect its metabolism, and ketoconazole and fluconazole, potent inhibitors of CYP3A and 2C9, respectively, have been shown to have no effect on eprosartan pharmacokinetics. Ranitidine also has no effect on eprosartan pharmacokinetics. Eprosartan (up to 400 mg b.i.d. or 800 mg q.d.) doses have been safely used concomitantly with a thiazide diuretic (hydrochlorothiazide). Eprosartan doses of up to 300 mg b.i.d. have been safely used concomitantly with sustained-release calcium channel blockers (sustained-release nifedipine) with no clinically significant adverse interactions. As with other drugs that block angiotensin II or its effects, concomitant use of potassium-sparing diuretics (e.g., spironolactone, triamterene, amiloride), potassium supplements or salt substitutes containing potassium may lead to increases in serum potassium (see PRECAUTIONS, Information for Patients, Potassium Supplements).

Non-Steroidal Anti-Inflammatory Agents including Selective Cyclooxygenase-2 Inhibitors (COX-2 Inhibitors)

In patients who are elderly, volume-depleted (including those on diuretic therapy), or with compromised renal function, co-administration of NSAIDs, including selective COX-2 inhibitors, with angiotensin II receptor antagonists, including eprosartan, may result in deterioration of renal function, including possible acute renal failure. These effects are usually reversible. Monitor renal function periodically in patients receiving eprosartan and NSAID therapy.

The antihypertensive effect of angiotensin II receptor antagonists, including eprosartan may be attenuated by NSAIDs including selective COX-2 inhibitors.

Hydrochlorothiazide: When administered concurrently the following drugs may interact with thiazide diuretics: Alcohol, barbiturates, or narcotics – potentiation of orthostatic hypotension may occur. Antidiabetic drug (oral agents and insulin) – dosage adjustment of the antidiabetic drug may be required. Other antihypertensive drugs – additive effect or potentiation. Cholestyramine and colestipol resins – Absorption of hydrochlorothiazide is impaired in the presence of anionic exchange resins. Single doses of either cholestyramine or colestipol resins bind the hydrochlorothiazide and reduce its absorption from the gastrointestinal tract by up to 85% and 43%, respectively. Corticosteroids, ACTH – intensified electrolyte depletion, particularly hypokalemia. Pressor amines (e.g., norepinephrine) – possible decreased response to pressor amines but not sufficient to preclude their use. Skeletal muscle relaxants, nondepolarizing (e.g., tubocurarine) – possible increased responsiveness to the muscle relaxant. Lithium – should not generally be given with diuretics. Diuretic agents reduce the renal clearance of lithium and add a high risk of lithium toxicity. Refer to the package insert for lithium preparations before use of such preparations with TEVETEN® HCT. Nonsteroidal Anti-Inflammatory Drugs – in some patients, the administration of a nonsteroidal anti-inflammatory agent can reduce the diuretic, natriuretic, and antihypertensive effects of loop, potassium-sparing and thiazide diuretics. Therefore, when TEVETEN® HCT and nonsteroidal anti-inflammatory agents are used concomitantly, the patient should be observed closely to determine if the desired effect of the diuretic is obtained.

Carcinogenesis, Mutagenesis, Impairment of Fertility

No carcinogenicity studies have been conducted with eprosartan mesylate in combination with hydrochlorothiazide. Eprosartan mesylate was not carcinogenic in dietary restricted rats or ad libitum fed mice dosed at 600 mg and 2000 mg eprosartan/kg/day, respectively, for up to 2 years. In male and female rats, the systemic exposure (AUC) to unbound eprosartan at the dose evaluated was only approximately 25% of the exposure achieved in humans given TEVETEN® HCT. In mice, the systemic exposure (AUC) to unbound eprosartan was approximately 35 times the exposure achieved in humans given TEVETEN® HCT. Two-year feeding studies in mice and rats conducted under the auspices of the National Toxicology Program (NTP) uncovered no evidence of a carcinogenic potential of hydrochlorothiazide in female mice (at doses of up to approximately 600 mg/kg/day) or in male and female rats (at doses of up to approximately 100 mg/kg/day). The NTP, however, found equivocal evidence for hepatocarcinogenicity in male mice. Eprosartan mesylate was not mutagenic in vitro in mammalian cells (mouse lymphoma assay). Eprosartan mesylate alone or in combination with hydrochlorothiazide was not mutagenic in vitro in bacteria (Ames test) and did not cause structural chromosomal damage in vivo (mouse micronucleus assay). In human peripheral lymphocytes in vitro, eprosartan mesylate in combination with hydrochlorothiazide was positive for clastogenicity with and without metabolic activation. In the same assay, eprosartan mesylate alone was associated with polyploidy but there was only equivocal evidence of structural chromosomal damage. Hydrochlorothiazide was not genotoxic in vitro in the Ames test and in the Chinese Hamster Ovary (CHO) test for chromosomal aberrations, or in vivo in assays using mouse germinal cell chromosomes, Chinese hamster bone marrow chromosomes, and the Drosophila sex-linked recessive lethal trait gene. Positive test results were obtained in the in vitro CHO Sister Chromatid Exchange (clastogenicity) and Mouse Lymphoma Cell (mutagenicity) assays and in the Aspergillus nidulans non-disjunction assay. No fertility studies have been conducted with eprosartan mesylate in combination with hydrochlorothiazide. Eprosartan mesylate had no adverse effects on the reproductive performance of male or female rats at oral doses up to 1000 mg eprosartan/kg/day. Hydrochlorothiazide had no adverse effects on the fertility of mice and rats of either sex in studies wherein these species were exposed, via their diet, to doses of up to 100 and 4 mg/kg/day, respectively, prior to conception and throughout gestation.

Pregnancy

Pregnancy Category C (first trimester) and D (second and third trimesters): See WARNINGS: Fetal/Neonatal Morbidity and Mortality.

Nursing Mothers

Eprosartan is excreted in animal milk; it is not known whether eprosartan is excreted in human milk. Because many drugs are excreted in human milk and because of the potential for serious adverse reactions in nursing infants from eprosartan, a decision should be made whether to discontinue nursing or to discontinue the drug, taking into account the importance of the drug to the mother. Thiazides appear in human milk. Because of the potential for adverse effects on the nursing infant, a decision should be made whether to discontinue nursing or discontinue the drug, taking into account the importance of the drug to the mother.

Pediatric Use

Safety and effectiveness in pediatric patients have not been established.

Geriatric Use

In the controlled clinical trials where patients received eprosartan/hydrochlorothiazide combination therapy, 15% to 33% of the patients were 65 years of age or greater. There was no difference in the effect of TEVETEN® HCT 600/12.5 mg treatment according to age. However, following single oral dose administration of eprosartan to healthy elderly men, (aged 68 to 78 years), AUC, Cmax, and Tmax eprosartan values increased, on average, by approximately twofold, compared to healthy young men (aged 20 to 38 years) who received the same dose. (See Pharmacokinetics, Special Populations).

ADVERSE REACTIONS

TEVETEN® HCT 600/12.5 mg has been evaluated for safety in 268 patients in double-blind, controlled clinical trials. Most of these patients were treated with TEVETEN® HCT 600/12.5 mg for 29 to 60 days. Eprosartan/hydrochlorothiazide combination therapy has been evaluated for safety in 890 patients in open-label, long-term clinical trials. Approximately 50% of these patients were treated with eprosartan/hydrochlorothiazide for over 2 years. Eprosartan/hydrochlorothiazide combination therapy was well tolerated. Most adverse events were of mild or moderate severity and did not require discontinuation of therapy. Adverse experiences were similar in patients regardless of age, gender, or race. In the controlled clinical trials, about 3% of the 268 patients treated with TEVETEN® HCT 600/12.5 mg discontinued therapy due to clinical adverse experiences.

Adverse Events Occurring at an Incidence of Greater Than 3% Among TEVETEN® HCT Treated Patients

The following table lists adverse events that occurred at an incidence of >3% among TEVETEN® HCT 600/12.5 mg- or monotherapy-treated patients who participated in the controlled clinical trials. Of the 268 patients who received TEVETEN® HCT 600/12.5 mg during the double-blind treatment period in the controlled trials, 110 patients were reported to have adverse events.

Table 1 Incidence of Adverse Events >3% During the Double-Blind Treatment Period by Preferred Term and Treatment Grouping: Controlled Studies
 | Placebo (N=246) | Eprosartan 600 mg (N=275) | HCTZ 12.5 mg (N=117) | HCTZ 25 mg (N=52) | Eprosartan 600 mg/HCTZ 12.5 mg (N=268)
Preferred Term | n (%) | n (%) | n (%) | n (%) | n (%)
Dizziness | 4 (1.6) | 5 (1.8) | 2 (1.7) | 2 (3.8) | 11 (4.1)
Headache | 22 (8.9) | 10 (3.6) | 4 (3.4) | 3 (5.8) | 9 (3.4)
Back pain | 6 (2.4) | 7 (2.5) | 2 (1.7) | 2 (3.8) | 7 (2.6)
Fatigue | 6 (2.4) | 5 (1.8) | 1 (0.9) | 2 (3.8) | 5 (1.9)
Myalgia | 8 (3.3) | 2 (0.7) | 3 (2.6) | 0 (0.0) | 1 (0.4)
Upper Respiratory Tract Infection | 8 (3.3) | 2 (0.7) | 0 (0.0) | 2 (3.8) | 1 (0.4)
Sinusitis | 4 (1.6) | 1 (0.4) | 0 (0.0) | 2 (3.8) | 0 (0.0)
Viral Infection | 4 (1.6) | 0 (0.0) | 2 (1.7) | 2 (3.8) | 0 (0.0)

The adverse events reported in over 600 patients that received TEVETEN®/hydrochlorothiazide combination therapy for at least 1 year in the open-label, long-term clinical trials were comparable to those reported in the controlled trials.

Eprosartan Mesylate: In addition to the adverse events above, potentially important adverse events that are included in the current labeling for TEVETEN® monotherapy are listed below. Most of these adverse events occurred in <1% of patients, or were as frequent or more frequent in the placebo group. It is not known if these events were related to eprosartan usage: Body as a Whole: alcohol intolerance, asthenia, substernal chest pain, dependent edema, peripheral edema, facial edema, fatigue, fever, hot flushes, influenza-like symptoms, injury, malaise, pain, rigors, viral infection; Cardiovascular: angina pectoris, bradycardia, abnormal ECG, specific abnormal ECG, extrasystoles, atrial fibrillation, hypotension (including orthostatic hypotension), tachycardia, palpitations; Gastrointestinal: abdominal pain, anorexia, constipation, diarrhea, dry mouth, dyspepsia, esophagitis, flatulence, gastritis, gastroenteritis, gingivitis, nausea, periodontitis, toothache, vomiting; Hematologic: anemia, purpura; Liver and Biliary: increased SGOT, increased SGPT; Metabolic and Nutritional: increased creatine phosphokinase, diabetes mellitus, glycosuria, gout, hypercholesterolemia, hyperglycemia, hyperkalemia, hypokalemia, hyponatremia, hypertriglyceridemia; Musculoskeletal: arthralgia, arthritis, aggravated arthritis, arthrosis, skeletal pain, tendinitis; Nervous System/Psychiatric: anxiety, ataxia, depression, dizziness, insomnia, migraine, neuritis, nervousness, paresthesia, somnolence, tremor, vertigo; Resistance Mechanism: herpes simplex, otitis externa, otitis media, upper respiratory tract infection; Respiratory: asthma, bronchitis, coughing, epistaxis, pharyngitis, rhinitis; Skin and Appendages: eczema, furunculosis, pruritus, rash, maculopapular rash, increased sweating; Special Senses: conjunctivitis, abnormal vision, xerophthalmia, tinnitus; Urinary: albuminuria, cystitis, hematuria, micturition frequency, polyuria, renal calculus, urinary incontinence, urinary tract infection; Vascular: leg cramps, peripheral ischemia.

Hydrochlorothiazide: Other adverse events that have been reported for hydrochlorothiazide, without regard to causality, are listed below: Body as a Whole: weakness; Cardiovascular: hypotension (including orthostatic hypotension); Digestive: pancreatitis, jaundice (intrahepatic cholestatic jaundice), diarrhea, vomiting, sialadenitis, cramping, constipation, gastric irritation, nausea, anorexia; Hematologic: aplastic anemia, agranulocytosis, leukopenia, hemolytic anemia, thrombocytopenia; Hypersensitivity: anaphylactic reactions, necrotizing angiitis (vasculitis and cutaneous vasculitis), respiratory distress including pneumonitis, and pulmonary edema, photosensitivity, fever, urticaria, rash, purpura; Metabolic: electrolyte imbalance including hyponatremia, hypokalemia, and hypochloremic alkalosis, hyperglycemia, glycosuria, hyperuricemia; Musculoskeletal: muscle spasm; Nervous System/Psychiatric: vertigo, paresthesias, restlessness; Renal: renal failure, renal dysfunction, interstitial nephritis, azotemia; Skin: erythema multiform, including Stevens-Johnson syndrome, exfoliative dermatitis, including toxic epidermal necrolysis, alopecia; Special Senses: transient blurred vision, xanthopsia; Urogenital: impotence.

Laboratory Test Findings:

In placebo-controlled studies, clinically important changes in standard laboratory parameters were rarely associated with administration of TEVETEN®. Patients were rarely withdrawn from TEVETEN® because of laboratory test results. Laboratory test findings that have been reported for TEVETEN® are listed below: Creatinine, Blood Urea Nitrogen: Minor elevations in creatinine and in BUN occurred in 0.6% and 1.3%, respectively, of patients taking TEVETEN® and 0.9% and 0.3%, respectively, of patients given placebo in controlled clinical trials. Two patients were withdrawn from clinical trials for elevations in serum creatinine and BUN, and three additional patients were withdrawn for increases in serum creatinine. Liver Function Tests: Minor elevations of ALAT, ASAT, and alkaline phosphatase occurred for comparable percentages of patients taking TEVETEN® or placebo in controlled clinical trials. An elevated ALAT of >3.5 x ULN occurred in 0.1% of patients taking TEVETEN® (one patient) and in no patient given placebo in controlled clinical trials. Four patients were withdrawn from clinical trials for an elevation in liver function tests. Hemoglobin: A greater than 20% decrease in hemoglobin was observed in 0.1% of patients taking TEVETEN® (one patient) and in no patient given placebo in controlled clinical trials. Two patients were withdrawn from clinical trials for anemia. Leukopenia: A WBC count of ≤3.0 x 10^3/mm^3 occurred in 0.3% of patients taking TEVETEN® and in 0.3% of patients given placebo in controlled clinical trials. One patient was withdrawn from clinical trials for leukopenia. Neutropenia: A neutrophil count of ≤1.5 x 10^3/mm^3 occurred in 1.3% of patients taking TEVETEN® and in 1.4% of patients given placebo in controlled clinical trials. No patient was withdrawn from any clinical trials for neutropenia. Thrombocytopenia: A platelet count of ≤100 x 10^9/L occurred in 0.3% of patients taking TEVETEN® (one patient) and in no patient given placebo in controlled clinical trials. Four patients receiving TEVETEN® in clinical trials were withdrawn for thrombocytopenia. In one case, thrombocytopenia was present prior to dosing with TEVETEN®. Serum Potassium: A potassium value of ≥5.6 mmol/L occurred in 0.9% of patients taking TEVETEN® and 0.3% of patients given placebo in controlled clinical trials. One patient was withdrawn from clinical trials for hyperkalemia and three for hypokalemia.

Additional Information:

Among the adverse events reported for patients receiving either TEVETEN® monotherapy or TEVETEN®/hydrochlorothiazide combination therapy in the TEVETEN® HCT clinical trials, some adverse events are not included in the current labeling for either TEVETEN® or hydrochlorothiazide monotherapy. The adverse events which are not currently included in the labeling for TEVETEN® or hydrochlorothiazide monotherapy include the following: angioedema, bilirubinemia, blood urea nitrogen increased, edema periorbital, eosinophilia, and NPN increased. The majority of these adverse events were reported in the open-label, long-term trials and were reported in small numbers of patients receiving TEVETEN® alone or TEVETEN® in combination with hydrochlorothiazide. All of these adverse events were either not reported in patients receiving TEVETEN® monotherapy or combination therapy with hydrochlorothiazide during the double-blind period of the controlled trials, or were reported at an incidence of ≤1% or in only one patient per treatment group in the controlled trials. The overall safety profile of the TEVETEN®/hydrochlorothiazide combination treatment is as expected based on the safety profile of each of the components and what is generally known about the patient population.

OVERDOSAGE

Eprosartan Mesylate: Limited data are available regarding overdosage. Appropriate symptomatic and supportive therapy should be given if overdosage should occur. There was no mortality in rats and mice receiving oral doses of up to 3000 mg eprosartan/kg and in dogs receiving oral doses of up to 1000 mg eprosartan/kg.

Hydrochlorothiazide: The most common signs and symptoms observed are those caused by electrolyte depletion (hypokalemia, hypochloremia, and hyponatremia) and dehydration resulting from excessive diuresis. If digitalis has also been administered, hypokalemia may accentuate cardiac arrhythmias. The degree to which hydrochlorothiazide is removed by hemodialysis has not been established. The oral LD50 of hydrochlorothiazide is greater than 10 g/kg in both mice and rats.

DOSAGE AND ADMINISTRATION

The usual recommended starting dose of eprosartan is 600 mg once daily when used as monotherapy in patients who are not volume-depleted (see WARNINGS, Hypotension in Volume- and/or Salt-Depleted Patients). Eprosartan can be administered once or twice daily and total daily doses ranging from 400 mg to 800 mg. There is limited experience with doses beyond 800 mg/day. If the antihypertensive effect measured at trough using once-daily monotherapy dosing is inadequate, a twice-a-day regimen at the same total daily dose or an increase in dose may give a more satisfactory response. Achievement of maximum blood pressure reduction in most patients may take 2 to 3 weeks. Hydrochlorothiazide is effective in doses of 12.5 mg to 50 mg once daily. To minimize dose-independent side effects, it is usually appropriate to begin combination therapy only after a patient has failed to achieve the desired effect with monotherapy. The side effects (see WARNINGS) of eprosartan are generally rare and apparently independent of dose; those of hydrochlorothiazide are a mixture of dose-dependent (primarily hypokalemia) and dose-independent (e.g., pancreatitis) phenomena, the former much more common than the latter. Therapy with any combination of eprosartan and hydrochlorothiazide will be associated with both sets of dose-independent side effects.

Replacement Therapy

TEVETEN® HCT may be substituted for the individual components. The usual recommended dose of TEVETEN® HCT is 600 mg/12.5 mg once daily when used as combination therapy in patients who are not volume-depleted (see WARNINGS, Hypotension in Volume-and/or Salt-Depleted Patients). If the antihypertensive effect measured at trough using TEVETEN® HCT 600/12.5 mg is inadequate, patients may be titrated to TEVETEN® HCT 600/25 mg once daily. Higher doses have not been studied in combination. Achievement of maximum blood pressure reduction in most patients may take 2 to 3 weeks. If the patient under treatment with TEVETEN® HCT requires additional blood pressure control at trough, or to maintain a twice a day dosing schedule of monotherapy, 300 mg TEVETEN® may be added as evening dose. TEVETEN® HCT may be used in combination with other antihypertensive agents such as calcium channel blockers if additional blood-pressure-lowering effect is required. Discontinuation of treatment with eprosartan does not lead to a rapid rebound increase in blood pressure.

Elderly, Hepatically Impaired or Renally Impaired Patients: No initial dosing adjustment is generally necessary for elderly or hepatically impaired patients or those with renal impairment. No initial dosing adjustment is generally necessary in patients with moderate and severe renal impairment with maximum dose not exceeding 600 mg daily. TEVETEN® HCT may be taken with or without food.

HOW SUPPLIED

TEVETEN® HCT is available as film-coated, capsule-shaped tablets, debossed with “SOLVAY” on one side and “5147” or “5150” on the other, supplied as bottles of 30 tablets as follows:

Eprosartan (mg) | HCTZ (mg) | Color | NDC
600 | 12.5 | Butterscotch | 54868-5281-1

STORAGE

Store at controlled room temperature 20° to 25°C (68° to 77°F) [see USP Controlled Room Temperature].

Abbott Laboratories

North Chicago, IL 60064 U.S.A.

©2010 Abbott Laboratories

Rev. April, 2011

Relabeling and Repackaging by:
Physicians Total Care, Inc.
Tulsa, OK 74146

PACKAGE LABEL

NDC 54868-5281-1

TEVETEN® HCT

eprosartan mesylate/hydrochlorothiazide

600/12.5 mg Tablets

Rx Only